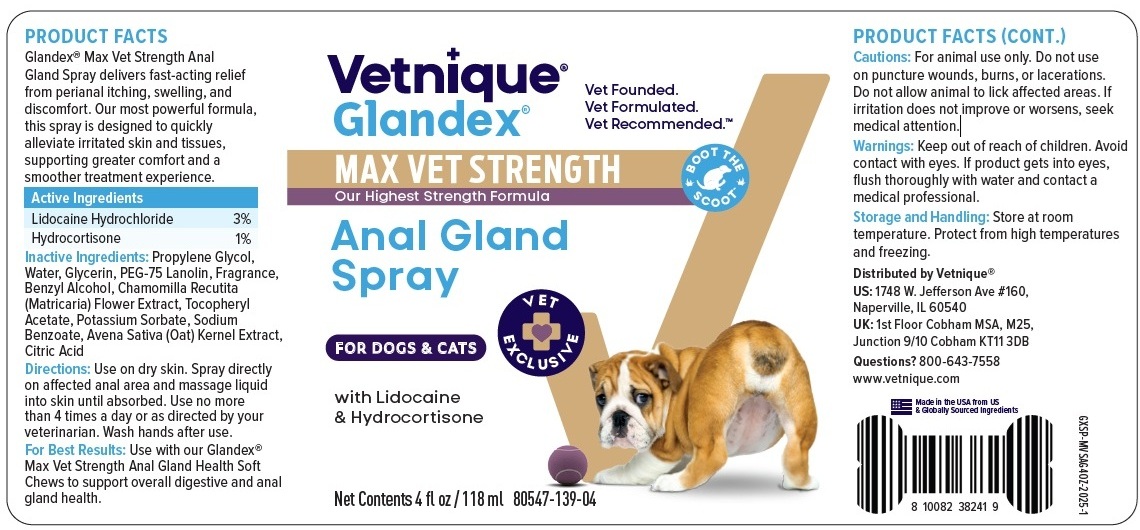 DRUG LABEL: Glandex MAX VET STRENGTH Anal Gland
NDC: 80547-139 | Form: SPRAY
Manufacturer: Vetnique Labs LLC
Category: animal | Type: OTC ANIMAL DRUG LABEL
Date: 20251022

ACTIVE INGREDIENTS: LIDOCAINE HYDROCHLORIDE 30 mg/1 mL; HYDROCORTISONE 10 mg/1 mL
INACTIVE INGREDIENTS: PROPYLENE GLYCOL; WATER; GLYCERIN; PEG-75 LANOLIN; BENZYL ALCOHOL; CHAMOMILE; .ALPHA.-TOCOPHEROL ACETATE; POTASSIUM SORBATE; SODIUM BENZOATE; OAT; CITRIC ACID MONOHYDRATE

Vetnique® Glandex® MAX VET STRENGTH Anal Gland Spray

PRODUCT FACTS

Glandex® Max Vet Strength Anal Gland Spray delivers fast-acting relief from perianal itching, swelling, and discomfort. Our most powerful formula, this spray is designed to quickly alleviate irritated skin and tissues, supporting greater comfort and a smoother treatment experience.

Active Ingredients

Lidocaine Hydrochloride 3%

Hydrocortisone 1%

Inactive Ingredients:

Propylene Glycol,Water, Glycerin, PEG-75 Lanolin, Fragrance, Benzyl Alcohol, Chamomilla Recutita(Matricaria) Flower Extract, Tocopheryl Acetate, Potassium Sorbate, Sodium Benzoate, Avena Sativa (Oat) Kernel Extract, Citric Acid

Directions:

Use on dry skin. Spray directly on affected anal area and massage liquid into skin until absorbed. Use no more than 4 times a day or as directed by your veterinrian. Wash hands after use.

For Best Results: Use with our Glandex® Max Vet Strength Anal Gland Health Soft Chews to support overall digestive and anal gland health.

Cautions:

For animal use only. Do not use on puncture wounds, burns, or lacerations. Do not allow animal to lick affected areas. If irritation does not improve or worsens, seek medical attention.

Warnings:

Keep out of reach of children. Avoid contact with eyes. If product gets into eyes, flush thoroughly with water and contact a medical professional.

Storage and Handling:

Store at room temperature. Protect from high temperatures and freezing.

Vet Founded.
Vet Formulated.
Vet Recommended.™

Our Highest Strength Formula

BOOT THE SCOOT

VET EXCLUSIVE

FOR DOGS & CATS

Distributed by Vetnique®
US: 1748 W. Jefferson Ave #160,
Naperville, IL 60540
UK: 1st Floor Cobham MSA, M25,
Junction 9/10 Cobham KT11 3DB

Questions? 800-643-7558
www.vetnique.com

Made in the USA from US
& Globally Sourced Ingredients